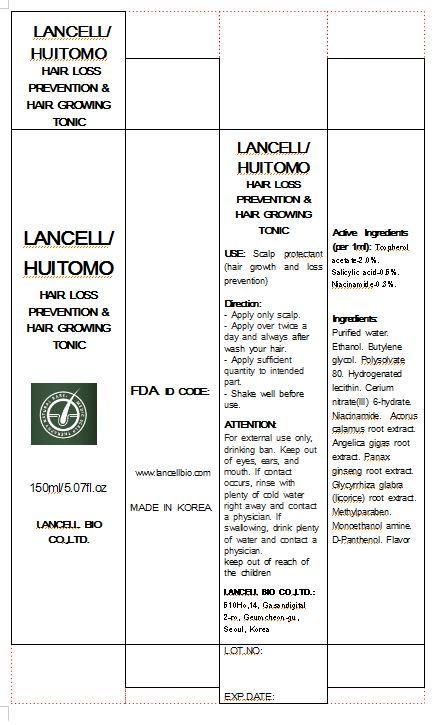 DRUG LABEL: LANCELL HUITOMO HAIR LOSS PREVENTION HAIR GROWING TONIC
NDC: 69388-2001 | Form: LIQUID
Manufacturer: Lancell Bio Co., Ltd.
Category: otc | Type: HUMAN OTC DRUG LABEL
Date: 20141201

ACTIVE INGREDIENTS: SALICYLIC ACID 0.5 g/100 mL
INACTIVE INGREDIENTS: WATER; NIACINAMIDE; .ALPHA.-TOCOPHEROL ACETATE

Drug Facts

ACTIVE INGREDIENT

salicylic acid

INACTIVE INGREDIENT

■Purified water ■Ethanol ■Butylene glycol ■Polysolvate 80 ■Hydrogenated lecithin ■Cerium nitrate(III) 6-hydrate ■Acorus calamus root extract ■Angelica gigas root extract ■Panax ginseng root extract ■Glycyrrhiza glabra (licorice) root extract ■Methylparaben ■Monoethanol amine ■D-Panthenol ■Flavor

PURPOSE

scalp protectant (hair growth and loss prevention)

keep out of reach of the children

INDICATIONS AND USAGE

■ Apply only scalp
■ Apply over twice a day and always after wash your hair
■ Apply sufficient quantity to intended part
■ Shake well before use

WARNINGS

For external use only, drinking ban
When using this product
■ keep out of eyes, ears, and mouth. If contact occurs, rinse with plenty of worm or cold water right away and in a serious situation, contact a physician. If swallowing, drink plenty of water and contact a physician
■ Keep out of reach of the children

DOSAGE AND ADMINISTRATION

for external use only